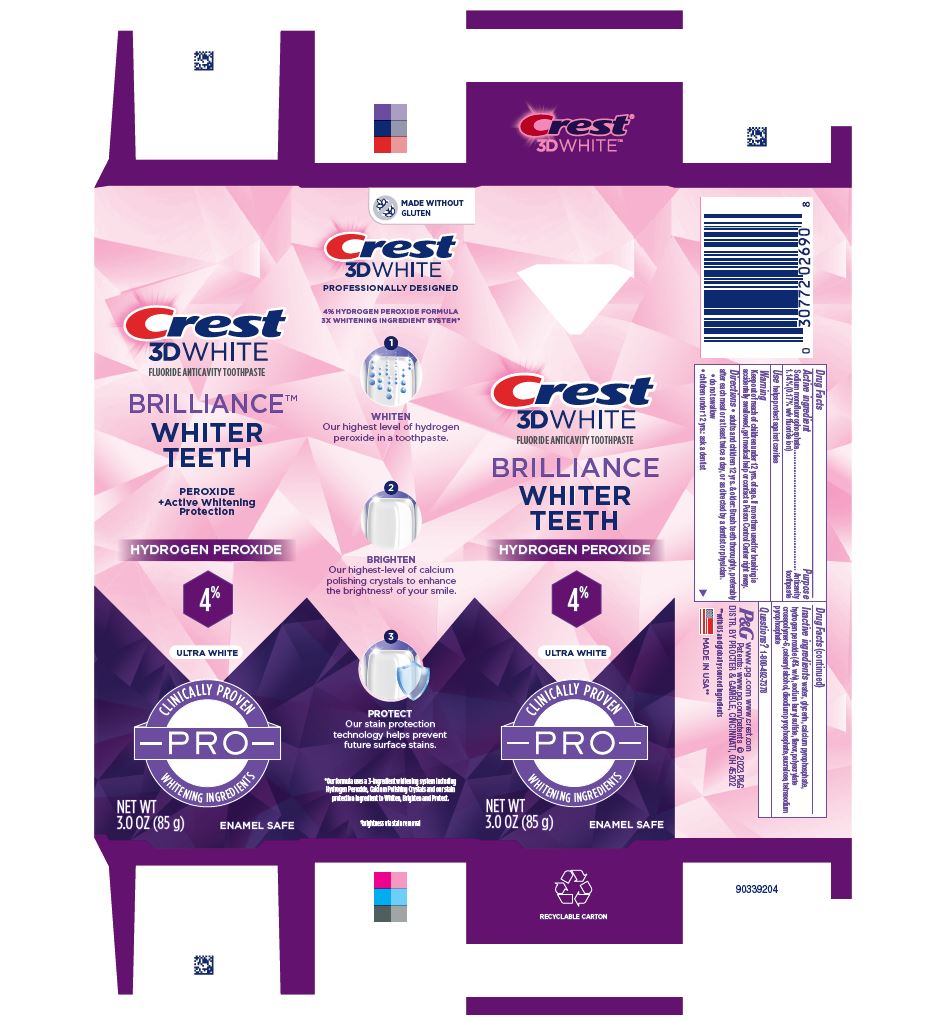 DRUG LABEL: Crest 3D White
NDC: 69423-760 | Form: PASTE, DENTIFRICE
Manufacturer: The Procter & Gamble Manufacturing Company
Category: otc | Type: HUMAN OTC DRUG LABEL
Date: 20260203

ACTIVE INGREDIENTS: SODIUM MONOFLUOROPHOSPHATE 1.7 mg/1 g
INACTIVE INGREDIENTS: AMMONIUM ACRYLOYLDIMETHYLTAURATE, DIMETHYLACRYLAMIDE, LAURYL METHACRYLATE AND LAURETH-4 METHACRYLATE COPOLYMER, TRIMETHYLOLPROPANE TRIACRYLATE CROSSLINKED (45000 MPA.S); CETOSTEARYL ALCOHOL; SODIUM PYROPHOSPHATE; GLYCERIN; HYDROGEN PEROXIDE; SODIUM LAURYL SULFATE; WATER; SUCRALOSE; CALCIUM PYROPHOSPHATE; SODIUM ACID PYROPHOSPHATE

Crest 3D White Brilliance Pro Ultra White Hydrogen Peroxide

Drug Facts

Sodium monofluorophosphate 1.14%

(0.17% w/v fluoride ion)

Purpose

Anticavity toothpaste

Use

helps protect against cavities

Warning

Keep out of reach of children under 12 yrs. of age. If more than used for brushing is accidentally swallowed, get medical help or contact a Poison Control Center right away.

Directions

- adults and children 12 yrs. & older: Brush teeth thoroughly, preferably after each meal or at least twice a day, or as directed by a dentist or physician.
- do not swallow
- children under 12 yrs.: ask a dentist

Inactive ingredients

water, glycerin, calcium pyrophosphate,
hydrogen peroxide (4% w/v), sodium lauryl sulfate, flavor, polyacrylate
crosspolymer-6, cetearyl alcohol, disodium pyrophosphate, sucralose, tetrasodium
pyrophosphate

Questions?

1-800-492-7378

DISTR. BY PROCTER & GAMBLE, CINCINNATI, OH 45202

Crest 3D White Ultra White 85g tube in carton

Crest

3D WHITE

FLUORIDE ANTICAVITY TOOTHPASTE

BRILLIANCE

WHITER TEETH

HYDROGEN PEROXIDE 4%

ULTRA WHITE

CLINICALLY PROVEN

-PRO-

WHITENING INGREDIENTS

NET WT 3.0 OZ (85 g)

ENAMEL SAFE